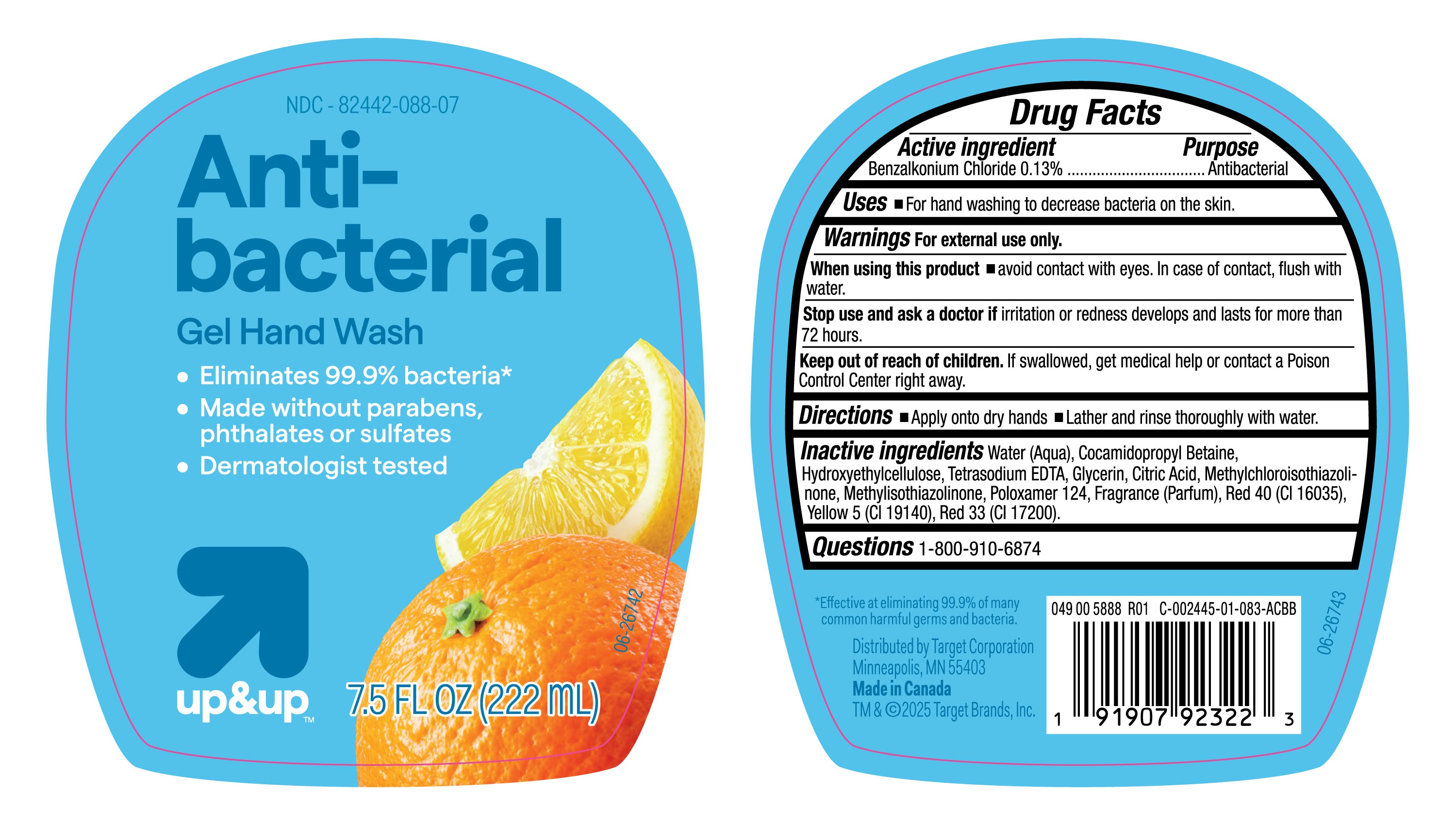 DRUG LABEL: UP and UP
NDC: 82442-088 | Form: LIQUID
Manufacturer: TARGET CORPORATION INC.
Category: otc | Type: HUMAN OTC DRUG LABEL
Date: 20251031

ACTIVE INGREDIENTS: BENZALKONIUM CHLORIDE 130 mg/100 mL
INACTIVE INGREDIENTS: WATER; HYDROXYETHYLCELLULOSE; FRAGRANCE CLEAN ORC0600327; RED 40; RED 33; POLOXAMER 124; COCAMIDOPROPYL BETAINE; TETRASODIUM EDTA; METHYLCHLOROISOTHIAZOLINONE; GLYCERIN; CITRIC ACID; YELLOW 5; METHYLISOTHIAZOLINONE

82442-088-07, Target up and up Antibacterial Liquid Hand Soap

Active Ingredient

Benzalkonium Chloride (0.13%)

Purpose

Antibacterial

Uses

- For hand washing to decrease bacteria on the skin.

Warnings

For external use only

When using this product

- Avoid contact with eyes. In case of contact, flush with water.

Stop use and ask a doctor

if irritation or redness develops and lasts for more than 72 hours.

Keep out of reach of children.

if swallowed, get medical help or contact a Poison Control center right away.

Directions

- Apply onto dry hands.
- Lather and rinse thoroughly with water.

Inactive Ingredients.

Water (Aqua), Cocamidopropyl Betaine, Hydroxyethylcellulose, Tetrasodium EDTA, Glycerin, Citric Acid, Methylchloroisothiazolinone, Methylisothiazolinone, Poloxamer 124, Fragrance (Parfum), Red 40 (CI 16035), Yellow 5 (CI 19140), Red 33 (CI 17200).

Questions

1-800-910-6874